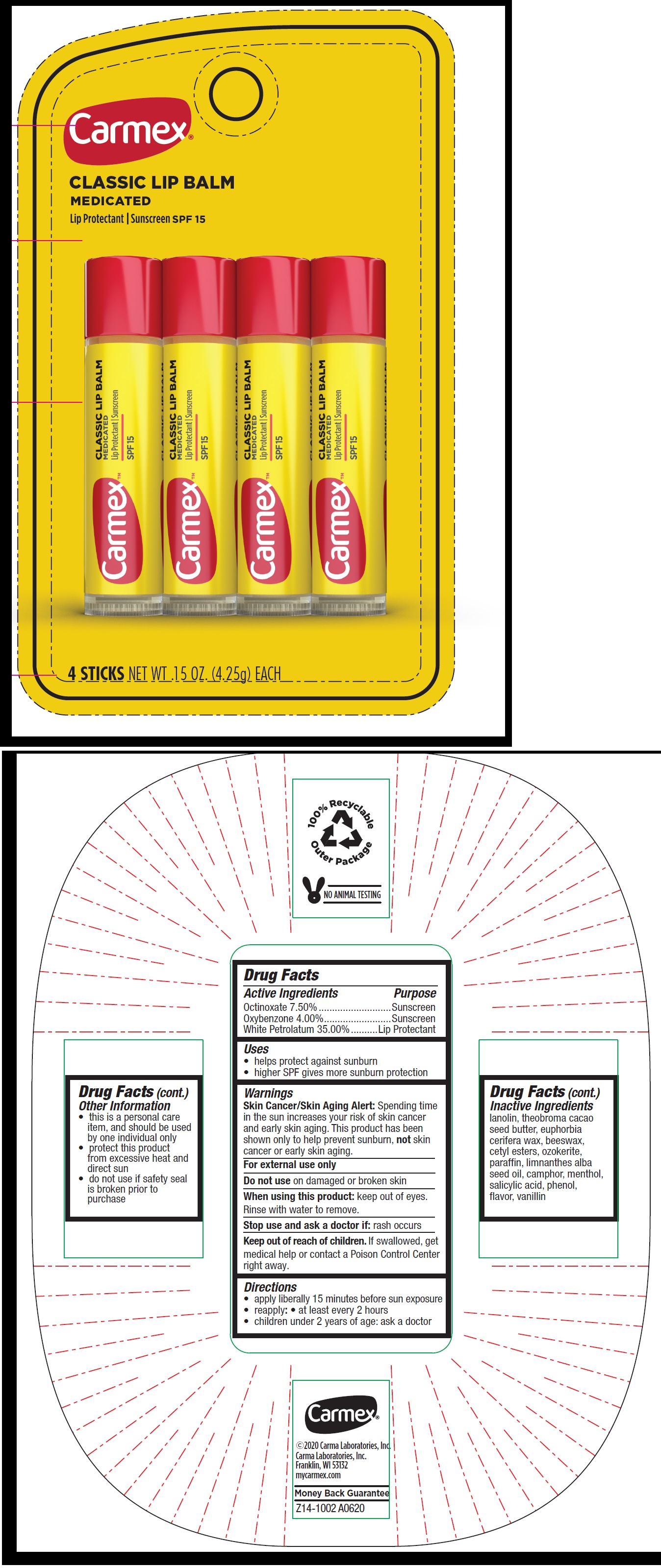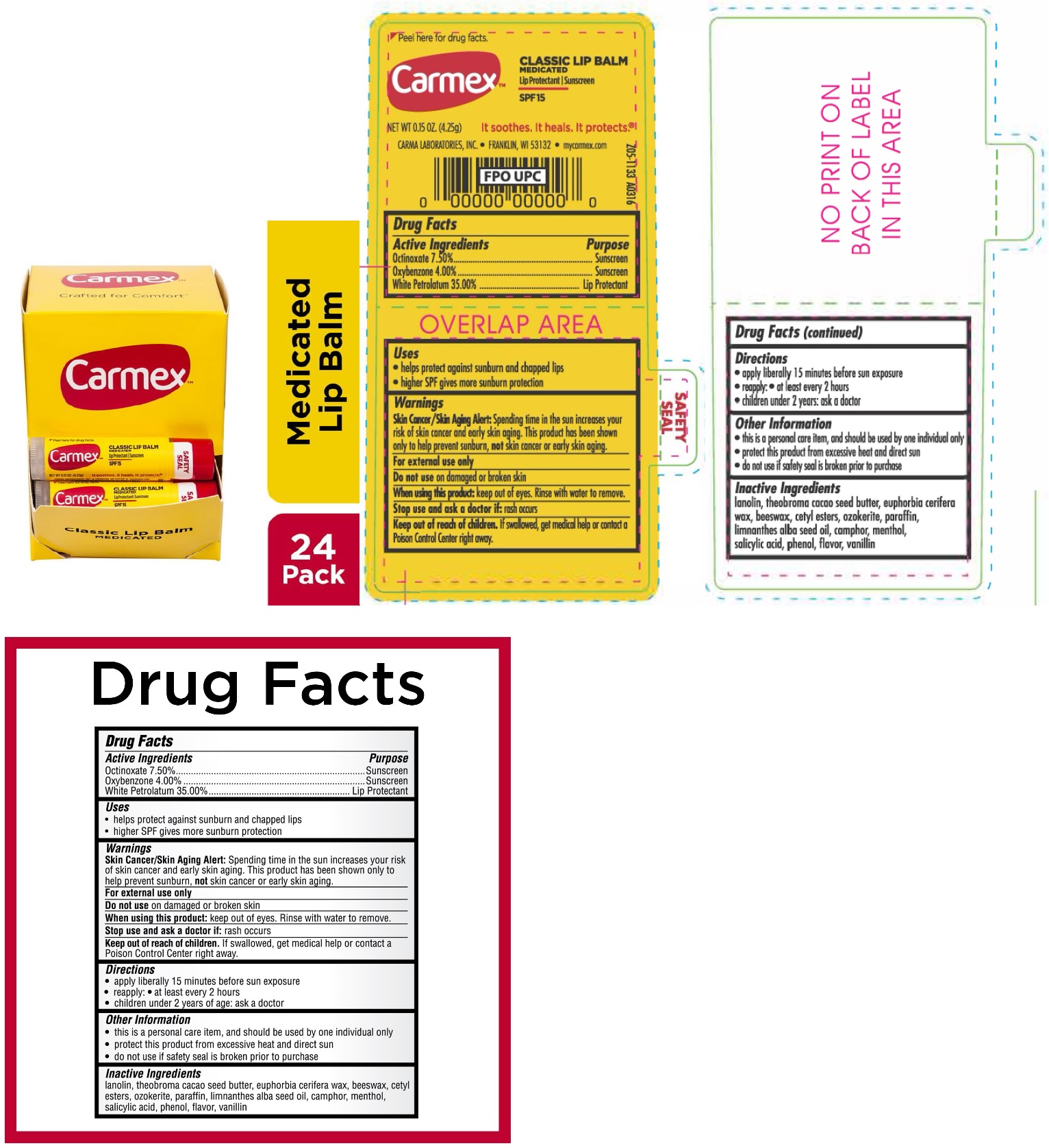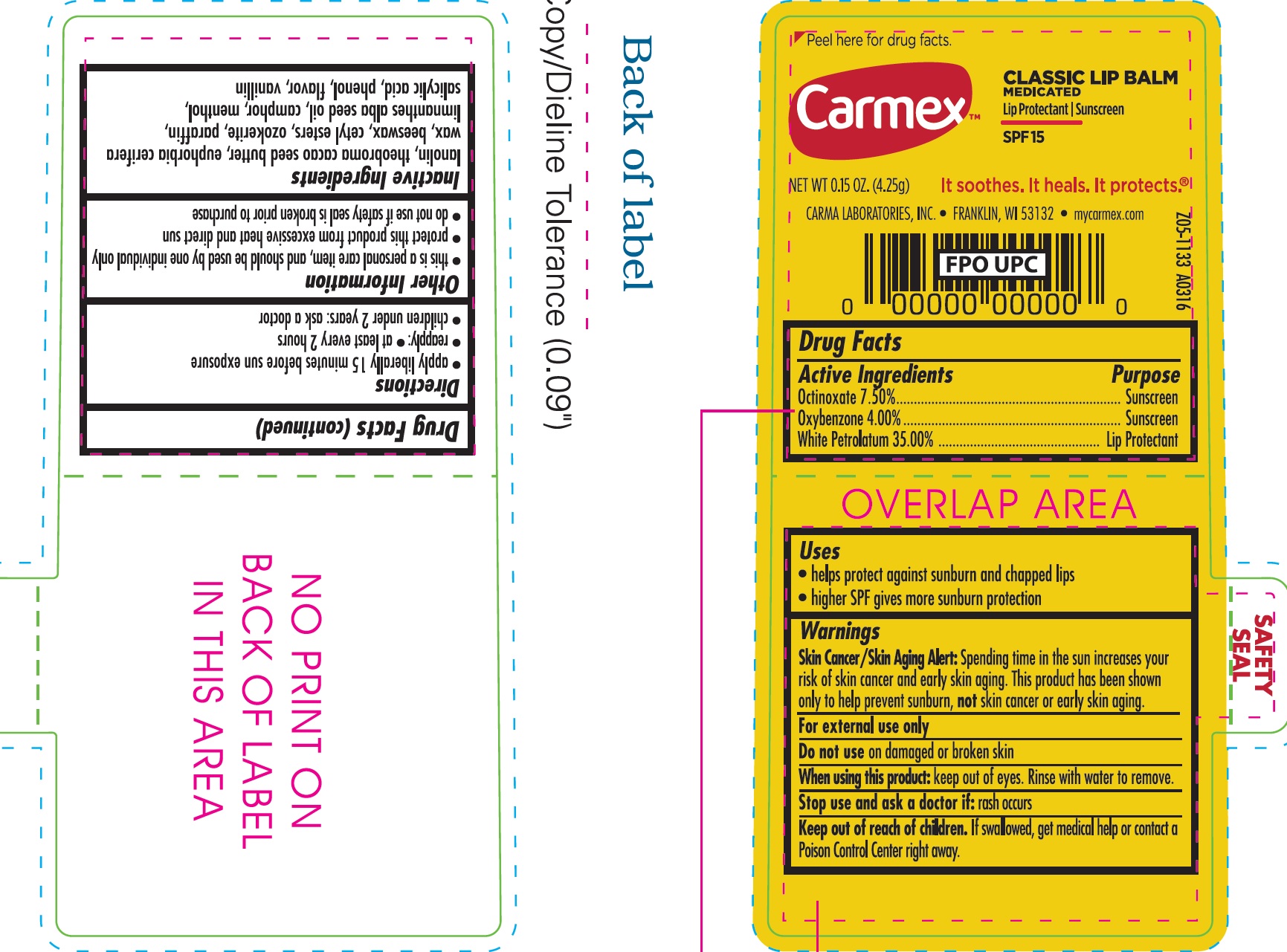 DRUG LABEL: Carmex Classic Lip Balm Medicated SPF 15
NDC: 10210-0023 | Form: SALVE
Manufacturer: Carma Laboratories, Inc.
Category: otc | Type: HUMAN OTC DRUG LABEL
Date: 20231025

ACTIVE INGREDIENTS: OCTINOXATE 7.5 g/100 g; OXYBENZONE 4 g/100 g; WHITE PETROLATUM 35 g/100 g
INACTIVE INGREDIENTS: LANOLIN; YELLOW WAX; CETYL ESTERS WAX; CERESIN; PARAFFIN; MEADOWFOAM SEED OIL; MENTHOL; SALICYLIC ACID; PHENOL; VANILLIN

Carmex Classic Lip Balm Medicated SPF 15

Active Ingredients

Octinoxate 7.50%

Oxybenzone 4.00%

White Petrolatum 35.00%

Purpose

Sunscreen

Lip Protectant

Uses

- helps protect against sunburn and chapped lips
- higher SPF gives more sunburn protection

Warnings

Spending time in the sun increases your risk of skin cancer and early skin aging. This product has been shown only to help prevent sunburn, not skin cancer or early skin aging. Skin Cancer/Skin Aging Alert:

For external use only

Do not use

on damaged or broken skin

When using this product:

- keep out of eyes. Rinse with water to remove.

Stop use and ask a doctor if:

rash occurs

Keep out of reach of children.

If swallowed, get medical help or contact a Poison Control Center right away.

Directions

- apply liberally 15 minutes before sun exposure
- reapply: • at least every 2 hours
- children under 2 years: ask a doctor

Other Information

- this is a personal care item, and should be used by one individual only
- protect this product from excessive heat and direct sun
- do not use if safety seal is broken prior to purchase

Inactive Ingredients

lanolin, theobroma cacao seed butter, euphorbia cerifera wax, beeswax, cetyl esters, ozokerite, paraffin, limnanthes alba seed oil, camphor, menthol, salicylic acid, phenol, flavor, vanillin